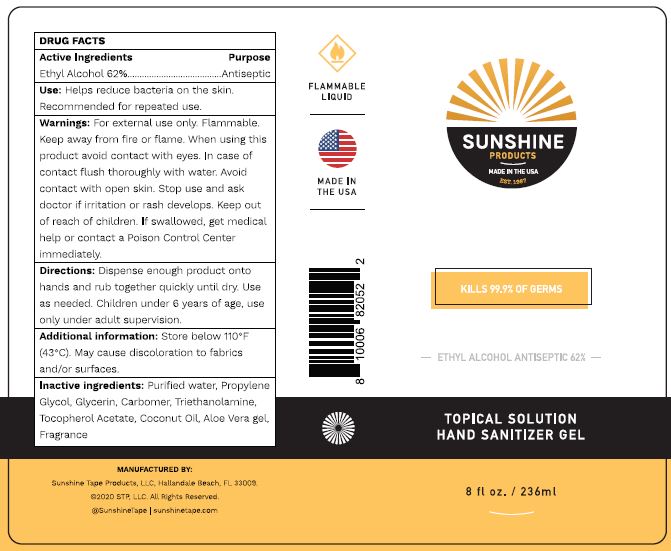 DRUG LABEL: HAND SANITIZER
NDC: 74598-111 | Form: GEL
Manufacturer: Sunshine Tape Products LLC
Category: otc | Type: HUMAN OTC DRUG LABEL
Date: 20200403

ACTIVE INGREDIENTS: ALCOHOL 62 mL/100 mL
INACTIVE INGREDIENTS: WATER; PROPYLENE GLYCOL; ALOE VERA LEAF; GLYCERIN; CARBOMER HOMOPOLYMER TYPE B (ALLYL PENTAERYTHRITOL OR ALLYL SUCROSE CROSSLINKED); TROLAMINE; .ALPHA.-TOCOPHEROL ACETATE; COCONUT OIL

HAND SANITIZER GEL

ACTIVE INGREDIENT

ETHYL ALCOHOL 62%

PURPOSE

ANTISEPTIC

USES

Helps reduce bacteria on the skin. Recommended for repeated use.

WARNINGS

For external use only. Flammable. Keep away from fire or flame. When using this product avoid contact with eyes. In case of contact flush thoroughly with water. Avoid contact with open skin. Stop use and ask doctor if irritation or rash develops.

Keep out of reach of children. If swallowed, get medical help or contact a Poison Control Center immediately.

DIRECTIONS

Dispense enough product onto hands and rub together quickly until dry. Use as needed. Children under 6 years of age, use only under adult supervision.

INACTIVE INGREDIENTS

Purified water, Propylene Glycol, Glycerin, Carbomer, Triethanolamine, Tocopherol Acetate, Coconut Oil, Aloe Vera gel, Fragrance